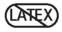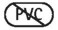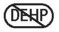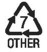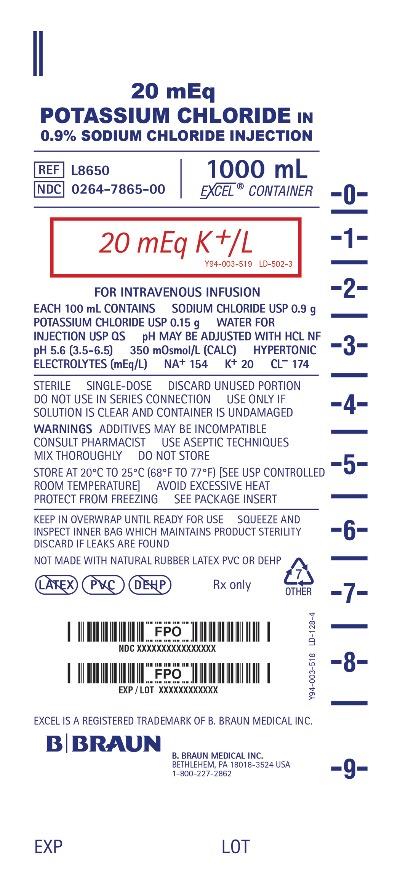 DRUG LABEL: POTASSIUM CHLORIDE IN SODIUM CHLORIDE
NDC: 0264-7865 | Form: SOLUTION
Manufacturer: B. Braun Medical Inc.
Category: prescription | Type: HUMAN PRESCRIPTION DRUG LABEL
Date: 20250711

ACTIVE INGREDIENTS: SODIUM CHLORIDE 0.9 g/100 mL; POTASSIUM CHLORIDE 0.15 g/100 mL
INACTIVE INGREDIENTS: WATER

Potassium Chloride in 0.9% Sodium Chloride Injection

DESCRIPTION

Each 100 mL of 20 mEq Potassium Chloride in 0.9% Sodium Chloride Injection (20 mEq K^+/L) contains: Sodium Chloride USP 0.9 g
Potassium Chloride USP 0.15 g; Water for Injection USP qs

pH may be adjusted with Hydrochloric Acid NF

pH: 5.6 (3.5–6.5) Calculated Osmolarity: 350 mOsmol/L

Concentration of Electrolytes (mEq/L):
Sodium 154 Potassium 20 Chloride 174

Potassium Chloride in 0.9% Sodium Chloride Injection is sterile, nonpyrogenic, hypertonic and contains no bacteriostatic or antimicrobial agents. This product is intended for intravenous administration.

The formulas of the active ingredients are:

Ingredients | Molecular Formula | Molecular Weight
Sodium Chloride USP | NaCl | 58.44
Potassium Chloride USP | KCl | 74.55

Not made with natural rubber latex, PVC or DEHP.

The plastic container is made from a multilayered film specifically developed for parenteral drugs. The solution contact layer is a rubberized copolymer of ethylene and propylene. The container is nontoxic and biologically inert. The container-solution unit is a closed system and is not dependent upon entry of external air during administration. The container is overwrapped to provide protection from the physical environment and to provide an additional moisture barrier when necessary.

Addition of medication should be accomplished using complete aseptic technique. The closure system has two ports; the one for the administration set has a tamper evident plastic protector and the other is a medication addition site. Refer to the Directions for Use of the container.

CLINICAL PHARMACOLOGY

Potassium Chloride in 0.9% Sodium Chloride Injection provides electrolytes and is a source of water for hydration. It is capable of inducing diuresis depending on the clinical condition of the patient.

Sodium, the major cation of the extracellular fluid, functions primarily in the control of water distribution, fluid balance, and osmotic pressure of body fluids. Sodium is also associated with chloride and bicarbonate in the regulation of acid-base equilibrium of body fluid.

Potassium, the principal cation of intracellular fluid, participates in carbohydrate utilization and protein synthesis, and is critical in the regulation of nerve conduction and muscle contraction, particularly in the heart.

Chloride, the major extracellular anion, closely follows the metabolism of sodium, and changes in the acid-base balance of the body are reflected by changes in the chloride concentration.

INDICATIONS AND USAGE

Potassium Chloride in 0.9% Sodium Chloride Injection is indicated for use in adults and pediatric patients as a source of electrolytes and water for hydration.

CONTRAINDICATIONS

Potassium Chloride in 0.9% Sodium Chloride Injection is contraindicated in clinical conditions where additives of sodium, potassium or chloride could be clinically detrimental.

WARNINGS

The administration of intravenous solutions can cause fluid and/or solute overload resulting in dilution of serum electrolyte concentrations, overhydration, congested states or pulmonary edema. The risk of dilutional states is inversely proportional to the electrolyte concentration. The risk of solute overload causing congested states with peripheral and pulmonary edema is directly proportional to the electrolyte concentration.

Solutions containing sodium ions should be used with great care, if at all, in patients with congestive heart failure, severe renal insufficiency, and in clinical states in which there is sodium retention with edema.

Infusion of isotonic (0.9%) sodium chloride during or immediately after surgery may result in excessive sodium retention. Use the patient's circulatory system status as a guide.

In patients with diminished renal function, administration of solutions containing sodium or potassium ions may result in sodium or potassium retention. Solutions containing potassium ions should be used with great care, if at all, in patients with hyperkalemia, severe renal failure, and in conditions in which potassium retention is present.

PRECAUTIONS

General

This solution should be used with care in patients with hypervolemia, renal insufficiency, urinary tract obstruction, or impending or frank cardiac decompensation.

Extraordinary electrolyte losses that may occur during protracted nasogastric suction, vomiting, diarrhea or gastrointestinal fistula drainage may necessitate additional electrolyte supplementation.

Additional essential electrolytes, minerals, and vitamins should be supplied as needed.

Sodium-containing solutions should be administered with caution to patients receiving corticosteroids or corticotropin, or to other salt-retaining patients. Infusion of more than one liter of isotonic (0.9%) sodium chloride may supply more sodium and chloride than normally found in serum, and can exceed normal tolerance, resulting in hypernatremia; this may also cause a loss of bicarbonate ions, resulting in an acidifying effect.

Potassium therapy should be guided primarily by serial electrocardiograms, especially in patients receiving digitalis. Serum potassium levels are not necessarily indicative of tissue potassium levels.

Solutions containing potassium should be used with caution in the presence of cardiac disease, particularly when accompanied by renal disease.

Care should be exercised in administering solutions containing sodium or potassium to patients with renal or cardiovascular insufficiency, with or without congestive heart failure, particularly if they are postoperative or elderly.

To minimize the risk of possible incompatibilities arising from mixing this solution with other additives that may be prescribed, the final infusate should be inspected for cloudiness or precipitation immediately after mixing, prior to administration, and periodically during administration.

Do not use plastic containers in series connection.

If administration is controlled by a pumping device, care must be taken to discontinue pumping action before the container runs dry or air embolism may result. If administration is not controlled by a pumping device, refrain from applying excessive pressure (>300mmHg) causing distortion to the container such as wringing or twisting. Such handling could result in breakage of the container.

This solution is intended for intravenous administration using sterile equipment. It is recommended that intravenous administration apparatus be replaced at least once every 24 hours.

Use only if solution is clear and container is undamaged.

Laboratory Tests

Clinical evaluation and periodic laboratory determinations are necessary to monitor changes in fluid balance, electrolyte concentrations, and acid-base balance during prolonged parenteral therapy or whenever the condition of the patient warrants such evaluation. Significant deviations from normal concentrations may require tailoring of the electrolyte pattern, in this or alternative solutions.

Carcinogenesis, Mutagenesis, Impairment of Fertility

Studies with Potassium Chloride in 0.9% Sodium Chloride Injection have not been performed to evaluate carcinogenic potential, mutagenic potential, or effects on fertility.

Pregnancy: Teratogenic Effects

Animal reproduction studies have not been conducted with Potassium Chloride in 0.9% Sodium Chloride Injection. It is also not known whether Potassium Chloride in 0.9% Sodium Chloride Injection can cause fetal harm when administered to a pregnant woman or can affect reproduction capacity. Potassium Chloride in 0.9% Sodium Chloride Injection should be given to a pregnant woman only if clearly needed.

Labor and Delivery

The effects of Potassium Chloride in 0.9% Sodium Chloride Injection on the duration of labor or delivery, on the possibility that forceps delivery or other intervention or resuscitation of the newborn will be necessary, and on the later growth, development, and functional maturation of the child are unknown. As reported in the literature, potassium containing solutions have been administered during labor and delivery. Caution should be exercised, and the fluid balance, glucose and electrolyte concentrations, and acid-base balance, of both mother and fetus should be evaluated periodically or whenever warranted by the condition of the patient or fetus.

Nursing Mothers

It is not known whether this drug is excreted in human milk. Because many drugs are excreted in human milk, caution should be exercised when Potassium Chloride in 0.9% Sodium Chloride Injection is administered to a nursing woman.

Pediatric Use

Safety and effectiveness of Potassium Chloride in Sodium Chloride Injection in pediatric patients has not been established by adequate and well-controlled studies. However, as referenced in the medical literature, potassium chloride injection has been used to treat pediatric patients with potassium deficiency when oral replacement therapy is not feasible.

For patients receiving potassium supplement at greater than maintenance rates, frequent monitoring of serum potassium levels and serial EKGs are recommended.

In neonates or in very small infants even small volumes of fluid may affect fluid and electrolyte balance. Care must be exercised in treatment of neonates, especially preterm neonates, whose renal function may be immature and whose ability to excrete fluid and solute loads may be limited. Fluid intake, urine output, and serum electrolytes should be monitored closely.

See WARNINGS and DOSAGE AND ADMINISTRATION.

Geriatric Use

Clinical studies of Potassium Chloride in Sodium Chloride Injection did not include sufficient numbers of subjects aged 65 and over to determine whether they respond differently from younger subjects. Other reported clinical experience has not identified differences in responses between elderly and younger patients.

In general, dose selection for an elderly patient should be cautious, usually starting at the low end of the dosing range, reflecting the greater frequency of decreased hepatic, renal, or cardiac function, and of concomitant disease or other drug therapy.

This drug is known to be substantially excreted by the kidney, and the risk of toxic reactions to this drug may be greater in patients with impaired renal function. Because elderly patients are more likely to have decreased renal function, care should be taken in dose selection, and it may be useful to monitor renal function.

See WARNINGS.

ADVERSE REACTIONS

Reactions which may occur because of the solution or the technique of administration include febrile response, infection at the site of injection, venous thrombosis or phlebitis extending from the site of injection, extravasation, and hypervolemia.

Too rapid infusion of hypertonic solutions may cause local pain and venous irritation. Rate of administration should be adjusted according to tolerance. Use of the largest peripheral vein and a small bore needle is recommended.

(See DOSAGE AND ADMINISTRATION.)

Symptoms may result from an excess or deficit of one or more of the ions present in the solution; therefore, frequent monitoring of electrolyte levels is essential.

Hypernatremia may be associated with edema and exacerbation of congestive heart failure due to the retention of water, resulting in an expanded extracellular fluid volume.

Reactions reported with the use of potassium-containing solutions include nausea, vomiting, abdominal pain and diarrhea. The signs and symptoms of potassium intoxication include paresthesias of the extremities, areflexia, muscular or respiratory paralysis, mental confusion, weakness, hypotension, cardiac arrhythmias, heart block, electrocardiographic abnormalities and cardiac arrest. Potassium deficits result in disruption of neuromuscular function, and intestinal ileus and dilatation.

If infused in large amounts, chloride ions may cause a loss of bicarbonate ions, resulting in an acidifying effect.

The physician should also be alert to the possibility of adverse reactions to drug additives. Prescribing information for drug additives to be administered in this manner should be consulted.

If an adverse reaction does occur, discontinue the infusion, evaluate the patient, institute appropriate therapeutic countermeasures and save the remainder of the fluid for examination if deemed necessary.

OVERDOSAGE

In the event of a fluid or solute overload during parenteral therapy, reevaluate the patient's condition and institute appropriate corrective treatment.

In the event of overdosage with potassium-containing solutions, discontinue the infusion immediately and institute corrective therapy to reduce serum potassium levels.

Treatment of hyperkalemia includes the following:

1. Dextrose Injection USP, 10% or 25% containing 10 units of crystalline insulin per 20 grams of dextrose administered intravenously, 300 to 500 mL per hour.
2. Absorption and exchange of potassium using sodium or ammonium cycle cation exchange resin, orally and as retention enema.
3. Hemodialysis and peritoneal dialysis. The use of potassium-containing foods or medications must be eliminated. However, in cases of digitalization, too rapid a lowering of plasma potassium concentration can cause digitalis toxicity.

DOSAGE AND ADMINISTRATION

This solution is for intravenous use.

Dosage is to be directed by a physician and is dependent upon age, weight, clinical condition of the patient and laboratory determinations. Frequent laboratory determinations and clinical evaluation are essential to monitor changes in blood glucose and electrolyte concentrations, and fluid and electrolyte balance during prolonged parenteral therapy.

When a hypertonic solution is to be administered peripherally, it should be slowly infused through a small bore needle, placed well within the lumen of a large vein to minimize venous irritation. Carefully avoid infiltration.

In the average adult, daily requirements of sodium and chloride are met by the infusion of one liter of 0.9% sodium chloride (154 mEq each of sodium and chloride).

Usually up to 40 mEq of potassium per liter daily is sufficient to replace normal loss in adults. Infusion rates should not exceed 10 mEq per hour or 120 mEq per day. A liter of fluid containing 40 mEq of potassium should be administered over an 8-hour period.

Fluid administration should be based on calculated maintenance or replacement fluid requirements for each patient.

Pediatric Dosage and Administration. There is no specific pediatric dose. The dose is dependent on weight, clinical condition and laboratory results.

See WARNINGS and PRECAUTIONS.

Some additives may be incompatible. Consult with pharmacist. When introducing additives, use aseptic techniques. Mix thoroughly. Do not store.

Parenteral drug products should be inspected visually for particulate matter and discoloration prior to administration, whenever solution and container permit.

HOW SUPPLIED

Potassium Chloride in 0.9% Sodium Chloride Injection is supplied sterile and nonpyrogenic in single-dose EXCEL® Containers packaged 12 per case.

NDC | REF | Size
20 mEq Potassium Chloride in 0.9% Sodium Chloride Injection
(20 mEq K^+/L)
0264-7865-00 | L8650 | 1000 mL

STORAGE AND HANDLING

Exposure of pharmaceutical products to heat should be minimized. Avoid excessive heat. Protect from freezing. Store at 20°C to 25°C (68°F to 77°F). Excursions permitted to 15°C to 30°C (59°F to 86°F). [See USP Controlled Room Temperature.]

Rx only

Revised: December 2025

EXCEL is a registered trademark of B. Braun Medical Inc.

Directions for Use of EXCEL Container

Caution: Do not use plastic containers in series connection.

To Open

Keep in overwrap until ready for use. Tear overwrap down at notch and remove solution container. Squeeze and inspect inner bag which maintains product sterility. Discard if leaks are found. If supplemental medication is desired, follow directions below before preparing for administration.

Note: Before use, perform the following checks:

Inspect each container. Read the label. Ensure solution is the one ordered and is within the expiration date.
Invert container and carefully inspect the solution in good light for cloudiness, haze, or particulate matter.
Any container which is suspect should not be used.
Use only if solution is clear and container is undamaged.

Preparation for Administration

1. Remove plastic protector from sterile set port at bottom of container.
2. Attach administration set. Refer to complete directions accompanying set.

To Add Medication

Warning: Some additives may be incompatible.

To Add Medication Before Solution Administration

1. Prepare medication site.
2. Using syringe with 18–22 gauge needle, puncture medication port and inner diaphragm and inject.
3. Squeeze and tap ports while ports are upright and mix solution and medication thoroughly.

To Add Medication During Solution Administration

1. Close clamp on the set.
2. Prepare medication site.
3. Using syringe with 18–22 gauge needle of appropriate length (at least 5/8 inch), puncture resealable medication port and inner diaphragm and inject.
4. Remove container from IV pole and/or turn to an upright position.
5. Evacuate both ports by tapping and squeezing them while container is in the upright position.
6. Mix solution and medication thoroughly.
7. Return container to in use position and continue administration.

B. Braun Medical Inc.
Bethlehem, PA 18018-3524 USA
1-800-227-2862

Y36-003-111 LD-234-6

PRINCIPAL DISPLAY PANEL - 1000 mL Container Label

20 mEq

POTASSIUM CHLORIDE IN

0.9% SODIUM CHLORIDE INJECTION

REF L8650

NDC 0264-7865-00

1000 mL

EXCEL® CONTAINER

20 mEq K^+/L

Y94-003-519 LD-502-3

FOR INTRAVENOUS INFUSION

EACH 100 mL CONTAINS SODIUM CHLORIDE USP 0.9 g

POTASSIUM CHLORIDE USP 0.15 g WATER FOR

INJECTION USP QS pH MAY BE ADJUSTED WITH HCL NF

pH 5.6 (3.5-6.5) 350 mOsmol/L (CALC) HYPERTONIC

ELECTROLYTES (mEq/L) NA^+ 154 K^+ 20 CL^– 174

STERILE SINGLE-DOSE DISCARD UNUSED PORTION

DO NOT USE IN SERIES CONNECTION USE ONLY IF

SOLUTION IS CLEAR AND CONTAINER IS UNDAMAGED

WARNINGS ADDITIVES MAY BE INCOMPATIBLE

CONSULT PHARMACIST USE ASEPTIC TECHNIQUES

MIX THOROUGHLY DO NOT STORE

STORE AT 20°C TO 25°C (68°F TO 77°F) [SEE USP CONTROLLED

ROOM TEMPERATURE] AVOID EXCESSIVE HEAT

PROTECT FROM FREEZING SEE PACKAGE INSERT

KEEP IN OVERWRAP UNTIL READY FOR USE SQUEEZE AND

INSPECT INNER BAG WHICH MAINTAINS PRODUCT STERILITY

DISCARD IF LEAKS ARE FOUND

NOT MADE WITH NATURAL RUBBER LATEX PVC OR DEHP

Rx only

EXCEL IS A REGISTERED TRADEMARK OF B. BRAUN MEDICAL INC.

B. BRAUN MEDICAL INC.
BETHLEHEM, PA 18018-3524 USA
1-800-227-2862

Y94-003-518 LD-128-4

EXP
LOT